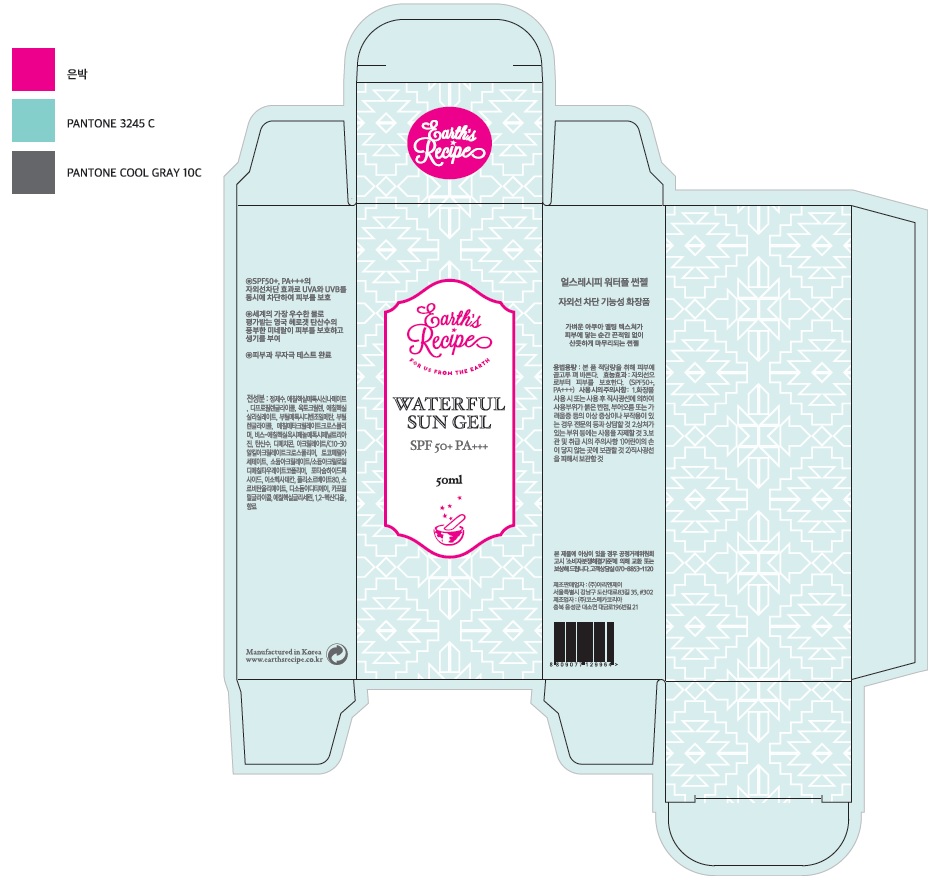 DRUG LABEL: Waterful Sun
NDC: 71496-0003 | Form: GEL
Manufacturer: ARI&J Inc
Category: otc | Type: HUMAN OTC DRUG LABEL
Date: 20170630

ACTIVE INGREDIENTS: OCTINOXATE 7 g/100 mL; OCTOCRYLENE 5 g/100 mL; OCTISALATE 4.5 g/100 mL; AVOBENZONE 4 g/100 mL
INACTIVE INGREDIENTS: WATER; BUTYLENE GLYCOL

ACTIVE INGREDIENT

Ethylhexyl Methoxycinnamate, Octocrylene, Ethylhexyl Salicylate, Butyl Methoxydibenzoylmethane

INACTIVE INGREDIENT

Water, Butylene Glycol, etc

PURPOSE

- Suncreen
- protects skin from UV rays
- if used as directed with other sun protection measures (see Directions), decreases the risk of skin cancer and early skin aging caused by the sun

keep out or reach of the children

INDICATIONS AND USAGE

apply generously 15 minutes before sun sxposure

reapply:

- after 80 minutes of swimming or sweating
- immediately after towel drying
- at least every two hours

Sun Protection Measures. Spending thime in the sun increases your risk of skin cancer and early skin aging. To decrease this risk, regularly use a sunscreen with a Broad Spectrum SPF value of 15 or higher and other sun protection measures including:

- limit time in the sun, expecially from 10 a.m. - 2 p.m.
- wear long-sleeved shirts, pants, hats, and sunglasses

children under 6 months of age: Ask a doctor

WARNINGS

- For external use only.
- Do not use on damaged or broken skin.
- When using this product keep out of eyes. Rinse with water to remove.
- Stop use and ask a doctor if rash occurs.
- Keep out of reach of children. If swallowed, get medical help or contact a Poison Control Center right away.
- do not place this product in this container in the excessive heat and direct sun.

DOSAGE AND ADMINISTRATION

for external use only